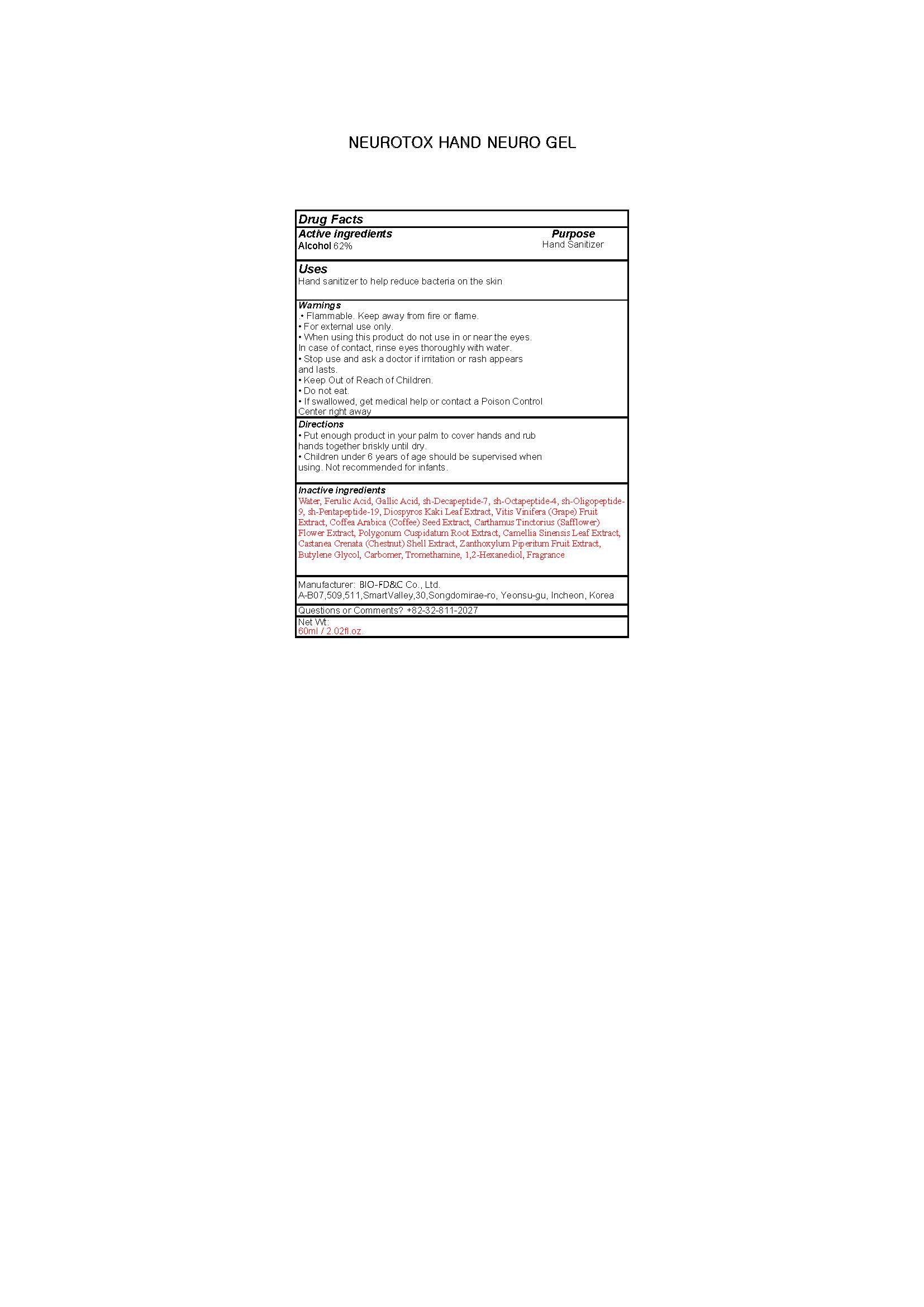 DRUG LABEL: NEUROTOX HAND NEURO
NDC: 76882-0002 | Form: GEL
Manufacturer: BIO-FD&C. Co., Ltd.
Category: otc | Type: HUMAN OTC DRUG LABEL
Date: 20200506

ACTIVE INGREDIENTS: ALCOHOL 37.2 mL/60 mL
INACTIVE INGREDIENTS: BUTYLENE GLYCOL; CARBOMER HOMOPOLYMER, UNSPECIFIED TYPE; WATER; 1,2-HEXANEDIOL

PACKAGE LABEL

PURPOSE

Antiseptic

ACTIVE INGREDIENT

Alcohol

INACTIVE INGREDIENT

Water, Ferulic Acid, Gallic Acid, sh Decapeptide 7, sh Octapeptide 4, sh Oligopeptide
9, sh Pentapeptide 19, Diospyros Kaki Leaf Extract, Vitis Vinifera (Grape) Fruit Extract, Coffea Arabica (Coffee) Seed Extract, Carthamus Tinctorius (Safflower) Flower Extract, Polygonum Cuspidatum Root Extract, Camellia Sinensis Leaf Extract, Castanea Crenata (Chestnut) Shell Extract, Zanthoxylum Piperitum Fruit Extract, Butylene Glycol, Carbomer, Tromethamine, 1,2 Hexanediol, Fragrance

DOSAGE AND ADMINISTRATION

For the external use only

WARNINGS

.• Flammable. Keep away from fire or flame.
• For external use only.
• When using this product do not use in or near the eyes.
In case of contact, rinse eyes thoroughly with water.
• Stop use and ask a doctor if irritation or rash appears
and lasts.
• Keep Out of Reach of Children.
• Do not eat.
• If swallowed, get medical help or contact a Poison Control
Center right away

Directions
• Put enough product in your palm to cover hands and rub
hands together briskly until dry.
• Children under 6 years of age should be supervised when
using. Not recommended for infants.

Keep out of reach of children